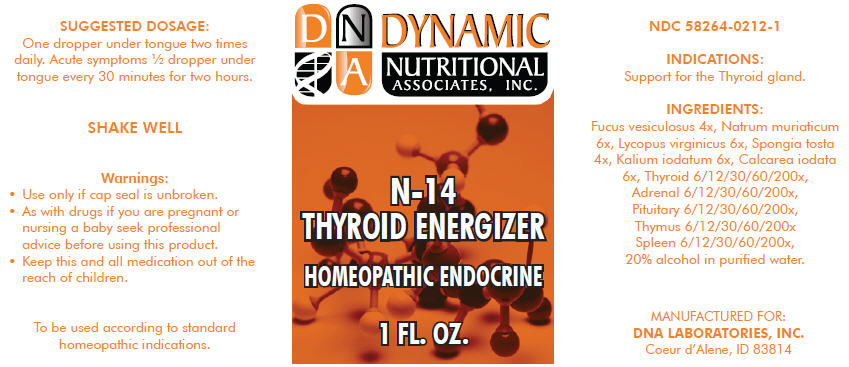 DRUG LABEL: N-14
NDC: 58264-0212 | Form: SOLUTION
Manufacturer: DNA Labs, Inc.
Category: homeopathic | Type: HUMAN OTC DRUG LABEL
Date: 20250109

ACTIVE INGREDIENTS: FUCUS VESICULOSUS 4 [hp_X]/1 mL; SODIUM CHLORIDE 6 [hp_X]/1 mL; LYCOPUS VIRGINICUS 6 [hp_X]/1 mL; SPONGIA OFFICINALIS SKELETON, ROASTED 4 [hp_X]/1 mL; POTASSIUM IODIDE 6 [hp_X]/1 mL; CALCIUM IODIDE 6 [hp_X]/1 mL; THYROID, UNSPECIFIED 200 [hp_X]/1 mL; BOS TAURUS ADRENAL GLAND 200 [hp_X]/1 mL; BOS TAURUS PITUITARY GLAND, POSTERIOR 200 [hp_X]/1 mL; BOS TAURUS THYMUS 200 [hp_X]/1 mL; SUS SCROFA SPLEEN 200 [hp_X]/1 mL
INACTIVE INGREDIENTS: ALCOHOL; WATER

N-14

NDC 58264-0212-1

INDICATIONS

PURPOSE

Support for the Thyroid gland.

ACTIVE INGREDIENT

INGREDIENTS

Fucus vesiculosus 4x, Natrum muriaticum 6x, Lycopus virginicus 6x, Spongia tosta 4x, Kalium iodatum 6x, Calcarea iodata 6x, Thyroid 6/12/30/60/200x, Adrenal 6/12/30/60/200x, Pituitary 6/12/30/60/200x, Thymus 6/12/30/60/200x Spleen 6/12/30/60/200x, 20% alcohol in purified water.

SUGGESTED DOSAGE

One dropper under tongue two times daily. Acute symptoms ½ dropper under tongue every 30 minutes for two hours.

STORAGE AND HANDLING

SHAKE WELL

Warnings

- Use only if cap seal is unbroken.

PREGNANCY OR BREAST FEEDING

- As with drugs if you are pregnant or nursing a baby seek professional advice before using this product.

KEEP OUT OF REACH OF CHILDREN

- Keep this and all medication out of the reach of children.

To be used according to standard homeopathic indications.

PRINCIPAL DISPLAY PANEL - 1 FL. OZ. Bottle Label

DYNAMIC
NUTRITIONAL
ASSOCIATES, INC.

N-14

THYROID ENERGIZER

HOMEOPATHIC ENDOCRINE

1 FL. OZ.